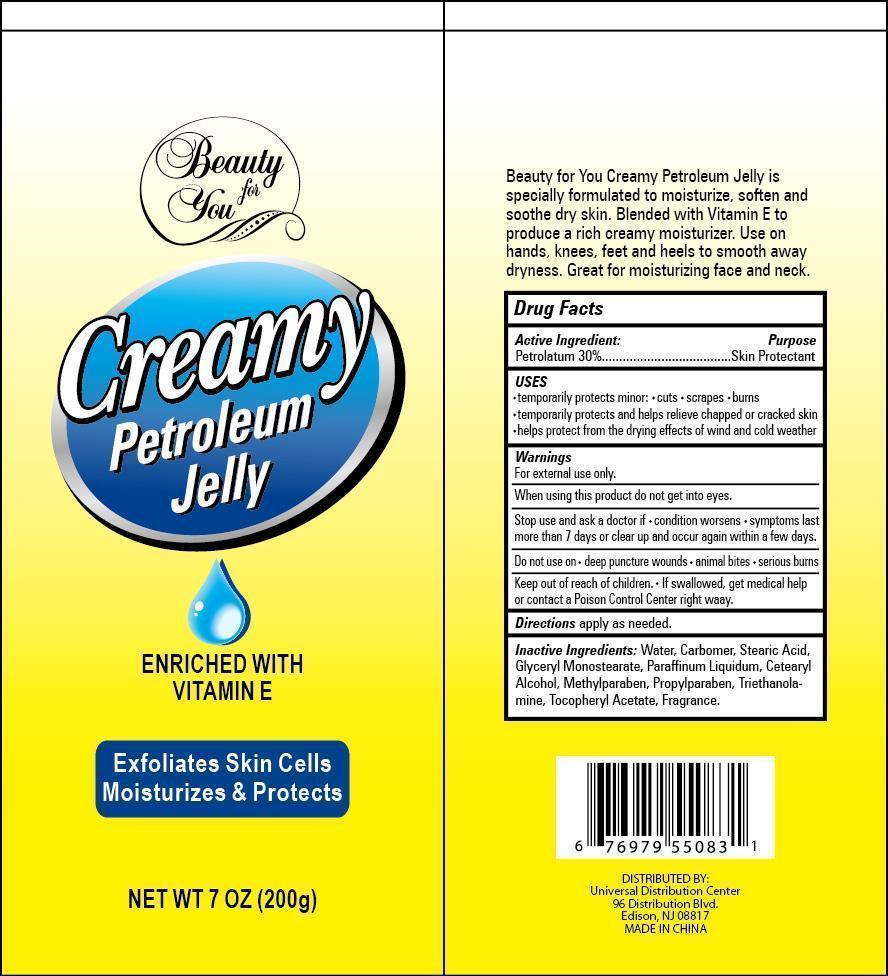 DRUG LABEL: Creamy Petroleum Jelly
NDC: 58503-063 | Form: JELLY
Manufacturer: China Ningbo Shangge Cosmetic Technology Corp.
Category: otc | Type: HUMAN OTC DRUG LABEL
Date: 20190913

ACTIVE INGREDIENTS: PETROLATUM 30 g/100 g
INACTIVE INGREDIENTS: WATER; CARBOMER COPOLYMER TYPE A (ALLYL PENTAERYTHRITOL CROSSLINKED); STEARIC ACID; GLYCERYL MONOSTEARATE; MINERAL OIL; CETOSTEARYL ALCOHOL; METHYLPARABEN; PROPYLPARABEN; TROLAMINE; .ALPHA.-TOCOPHEROL ACETATE

Creamy Petroleum Jelly

Active Ingredient Purpose

Petrolatum 30% .................................... Skin Protectant

PURPOSE

Beauty For You Creamy Petroleum Jelly

Enriched with Vitamin E

Exfoliates Skin Cells

Moisturizes & Protects

Net Wt 7 oz (200g)

Beauty For You Creamy Petroleum Jelly is specially formulated to moisturize, soften, and soothe dry skin. Blended with Vitamin E to produce a rich creamy moisturizer. Use on hands, knees, feet and heels to smooth away dryness. Great for moisturizing face and neck.

Keep out of reach of children. If swallowed, get medical help or contact a Poison Control Center right away.

Uses

- temporarily protects minor: cuts, scrapes, burns

- temporarily protects and helps relieve chapped or cracked skin

- helps protect from the drying effects of wind and cold weather

Warnings

for external use only.

when using this product do not get into eyes.

stop use and ask a doctor if: condition worsens, symptoms last more than 7 days or clear up and occur again within a few days.

do not use on: deep puncture wounds, animal bites, serious burns

Directions

apply as needed.

Inactive Ingredients

water, carbomer, stearic acid, glyceryl monostearate, paraffinum liquidum, cetearyl alcohol, methylparaben, propylparaben, triethanolamine, tocopheryl acetate, fragrance.